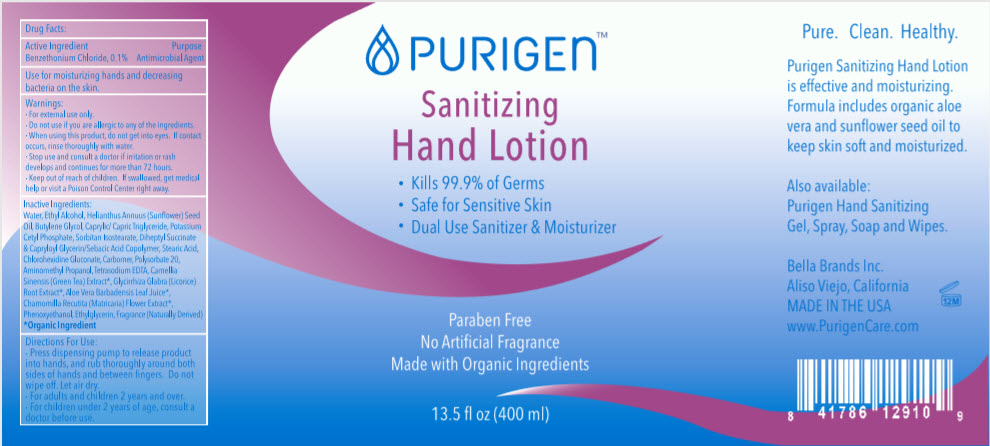 DRUG LABEL: Sanitizing Hand
NDC: 80994-002 | Form: LOTION
Manufacturer: BELLA BRANDS INC
Category: otc | Type: HUMAN OTC DRUG LABEL
Date: 20201118

ACTIVE INGREDIENTS: BENZETHONIUM CHLORIDE 0.1 g/100 mL
INACTIVE INGREDIENTS: WATER; ALCOHOL; SUNFLOWER OIL; BUTYLENE GLYCOL; MEDIUM-CHAIN TRIGLYCERIDES; POTASSIUM CETYL PHOSPHATE; SORBITAN ISOSTEARATE; STEARIC ACID; CARBOMER HOMOPOLYMER, UNSPECIFIED TYPE; POLYSORBATE 20; AMINOMETHYLPROPANOL; EDETATE SODIUM; GREEN TEA LEAF; LICORICE; CHAMOMILE; PHENOXYETHANOL; .ALPHA.-AMINOBUTYRIC ACID, L-

Sanitizing Hand

Drug Facts:

Active Ingredient

Benzethonium Chloride, 0.1%

Purpose

Antimicrobial Agent

Use

for moisturizing hands and decreasing bacteria on the skin.

Warnings

- For external use only.

- Do not use if you are allergic to any of the ingredients.

- When using this product, do not get into eyes. If contact occurs, rinse thoroughly with water.

- Stop use and consult a doctor if irritation or rash develops and continues for more than 72 hours.

- Keep out of reach of children. If swallowed, get medical help or visit a Poison Control Center right away.

Inactive Ingredients

Water, Ethyl Alcohol, Helianthus Annuus (Sunflower) Seed Oil, Butylene Glycol, Caprylic/ Capric Triglyceride, Potassium Cetyl Phosphate, Sorbitan Isostearate, Diheptyl Succinate & Capryloyl Glycerin/Sebacic Acid Copolymer, Stearic Acid, Chlorohexidine Gluconate, Carbomer, Polysorbate 20, Aminomethyl Propanol, Tetrasodium EDTA, Camellia Sinensis (Green Tea) Extract [Organic Ingredient] , Glycirrhiza Glabra (Licorice) Root Extract, Aloe Vera Barbadensis Leaf Juice, Chamomilla Recutita (Matricaria) Flower Extract, Phenoxyethanol, Ethylglycerin, Fragrance (Naturally Derived)

Directions For Use

- Press dispensing pump to release product into hands, and rub thoroughly around both sides of hands and between fingers. Do not wipe off. Let air dry.

- For adults and children 2 years and over.

- For children under 2 years of age, consult a doctor before use

PRINCIPAL DISPLAY PANEL - 400 ml Bottle Label

PURIGEN™

Sanitizing
Hand Lotion

- Kills 99.9% of Germs
- Safe for Sensitive Skin
- Dual Use Sanitizer & Moisturizer

Paraben Free
No Artificial Fragrance
Made with Organic Ingredients

13.5 fl oz (400 ml)